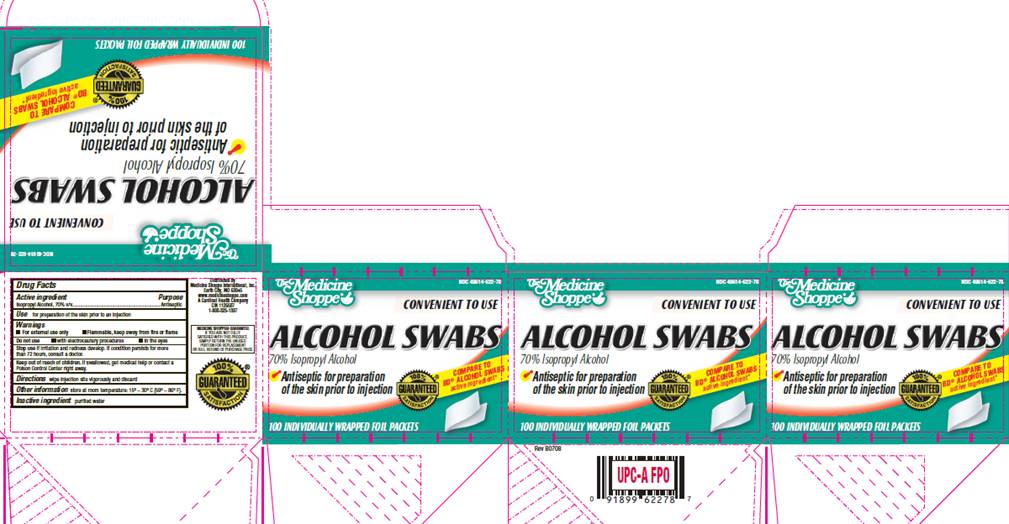 DRUG LABEL: Alcohol Pad
NDC: 49614-622 | Form: SWAB
Manufacturer: Medicine Shoppe International Inc
Category: otc | Type: HUMAN OTC DRUG LABEL
Date: 20100315

ACTIVE INGREDIENTS: Isopropyl alcohol 0.70 mL/1 1
INACTIVE INGREDIENTS: water

DRUG FACTS

ACTIVE INGREDIENT

Isopropyl Alcohol 70% v/v

PURPOSE

Antiseptic

USE

For preparation of the skin prior to an injection

WARNINGS

For external use only.
Flammable, keep away from fire or flame.

Do not use

- with electrocautery procedures
- in the eyes

Stop use

if irritation and redness develop. If condition persists for more than 72 hours, consult a doctor.

Keep out of reach of children

If swallowed, get medical help or contact a Poison Control Center right away.

DIRECTIONS

Wipe injection site vigorously and discard

OTHER INFORMATION

Store at room temperature 15° - 30° C (59° - 86° F)

INACTIVE INGREDIENT

purified water

PACKAGE INFORMATION

The Medicine Shoppe®
NDC 49614-622-78
CONVENIENT TO USE
ALCOHOL SWABS
70% Isopropyl Alcohol
Antiseptic for preparation
of the skin prior to injection
100% Satisfaction Guaranteed
COMPARE TO B-D® ALCOHOL SWABS active ingredient*
100 INDIVIDUALLY WRAPPED FOIL PACKETS
Distributed by
Medicine Shoppe International, Inc.
Earth City, MO 63045
www.medicineshoppe.com
A Cardinal Health Company
CIN 1126507
1-800-325-1397